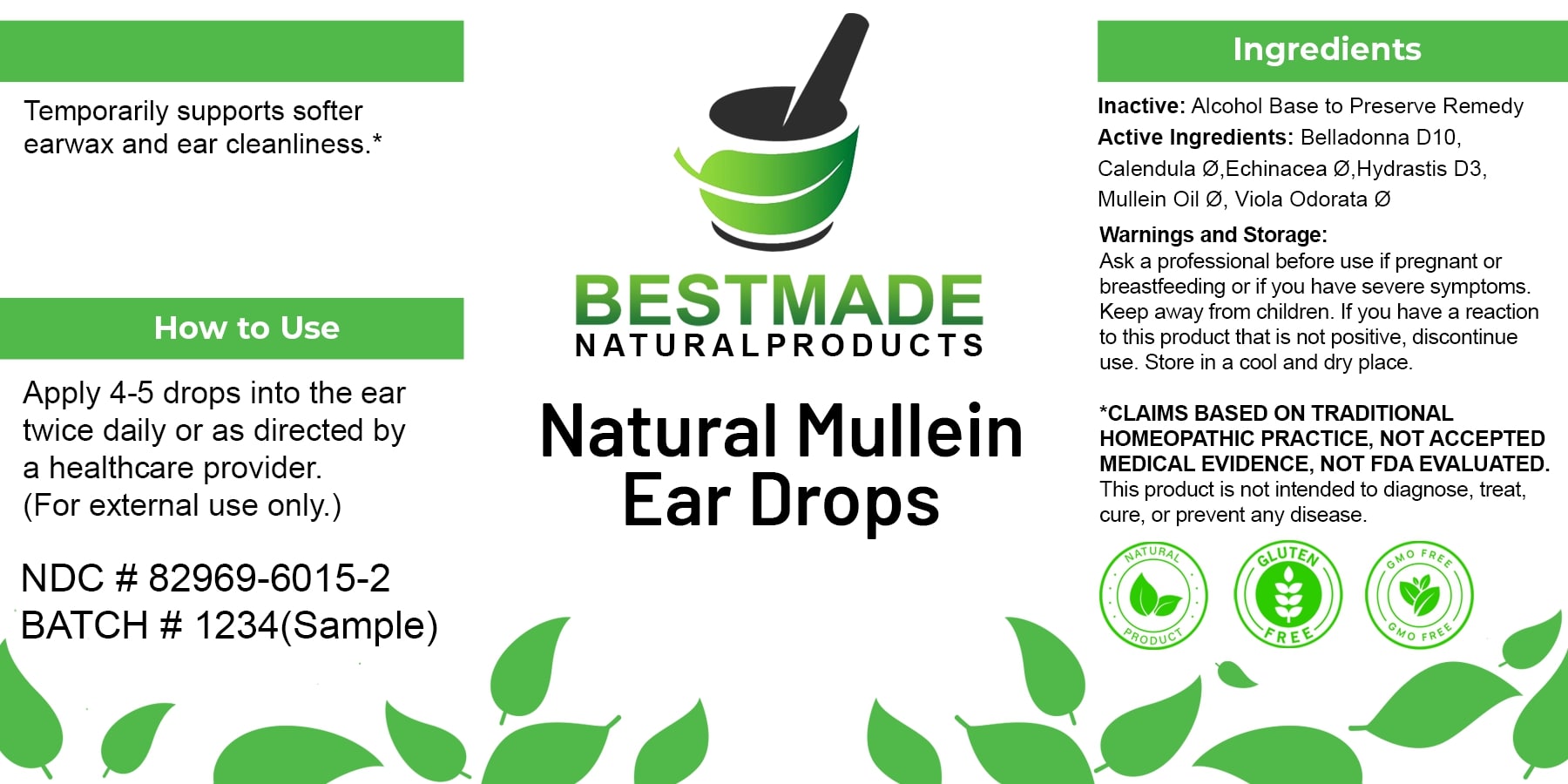 DRUG LABEL: Bestmade Natural Products - Mullein Ear Drops
NDC: 82969-6015 | Form: LIQUID
Manufacturer: Bestmade Natural Products
Category: homeopathic | Type: HUMAN OTC DRUG LABEL
Date: 20250527

ACTIVE INGREDIENTS: VERBASCUM THAPSUS 30 [hp_C]/30 [hp_C]; ATROPA BELLADONNA 30 [hp_C]/30 [hp_C]; CALENDULA OFFICINALIS FLOWERING TOP 30 [hp_C]/30 [hp_C]; VIOLA ODORATA WHOLE 30 [hp_C]/30 [hp_C]; ECHINACEA, UNSPECIFIED 30 [hp_C]/30 [hp_C]; GOLDENSEAL 30 [hp_C]/30 [hp_C]
INACTIVE INGREDIENTS: ALCOHOL 30 [hp_C]/30 [hp_C]

Mullein Ear Drops

DOSAGE AND ADMINISTRATION

How to Use

Apply 4-5 drops into the ear twice daily or as directed by a healthcare provider. (For external use only.)

Uses

Temporarily supports softer earwax and ear cleanliness.*

*CLAIMS BASED ON TRADITIONAL HOMEOPATHIC PRACTICE, NOT ACCEPTED MEDICAL EVIDENCE, NOT FDA EVALUATED.

This product is not intended to diagnose, treat, cure, or prevent any disease.

Inactive: Alcohol Base to Preserve Remedy

ACTIVE INGREDIENT

Belladonna D10: 0.008mL (HPUS)

Calendula Ø: 0.010mL (HPUS)

Echinacea Ø: 0.002mL (HPUS)

Hydrastis D3: 0.002mL (HPUS)

Mullein Oil Ø: 0.28mL (HPUS)

Viola Odorata Ø: 0.002mL (HPUS)

KEEP OUT OF REACH OF CHILDREN

Warnings and Storage:
Ask a professional before use if pregnant or breastfeeding or if you have severe symptoms.
Keep away from children. If you have a reaction to this product that is not positive, discontinue use. Store in a cool and dry place.

Uses

Temporarily supports softer earwax and ear cleanliness.*

*CLAIMS BASED ON TRADITIONAL HOMEOPATHIC PRACTICE, NOT ACCEPTED MEDICAL EVIDENCE, NOT FDA EVALUATED.

This product is not intended to diagnose, treat, cure, or prevent any disease.

Warnings and Storage:
Ask a professional before use if pregnant or breastfeeding or if you have severe symptoms.
Keep away from children. If you have a reaction to this product that is not positive, discontinue use. Store in a cool and dry place.
*CLAIMS BASED ON TRADITIONAL HOMEOPATHIC PRACTICE, NOT ACCEPTED MEDICAL EVIDENCE, NOT FDA EVALUATED.
This product is not intended to diagnose, treat, cure, or prevent any disease.

Entire package label